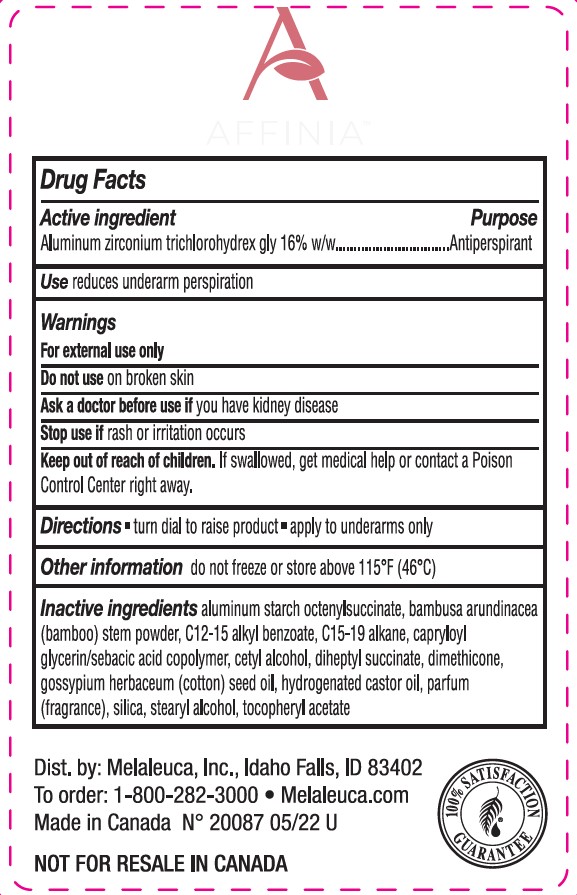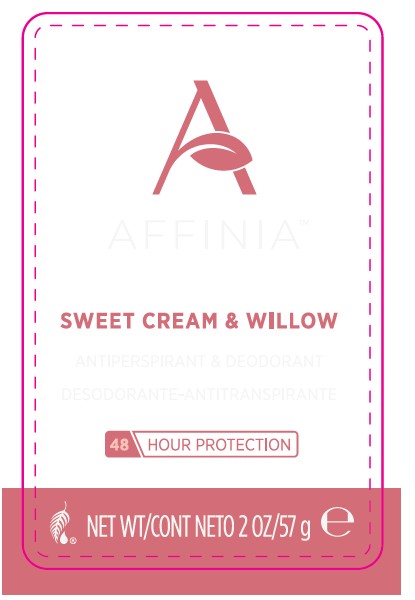 DRUG LABEL: Affinia Antiperspirant Deodorant
NDC: 54473-307 | Form: STICK
Manufacturer: Melaleuca Inc.
Category: otc | Type: HUMAN OTC DRUG LABEL
Date: 20250122

ACTIVE INGREDIENTS: ALUMINUM ZIRCONIUM TETRACHLOROHYDREX GLY 16 g/57 g
INACTIVE INGREDIENTS: BAMBUSA ARUNDINACEA STEM; STEARYL ALCOHOL; CAPRYLOYL GLYCERIN/SEBACIC ACID COPOLYMER (2000 MPA.S); ALUMINUM STARCH OCTENYLSUCCINATE; ALKYL (C12-15) BENZOATE; DIMETHICONE 100; DIHEPTYL SUCCINATE; HYDROGENATED CASTOR OIL; GOSSYPIUM HERBACEUM SEED RESIN; .ALPHA.-TOCOPHEROL ACETATE; C15-19 ALKANE; CETYL ALCOHOL; SILICON DIOXIDE

Affinia Antiperspirant Deodorant Sweet Cream & Willow